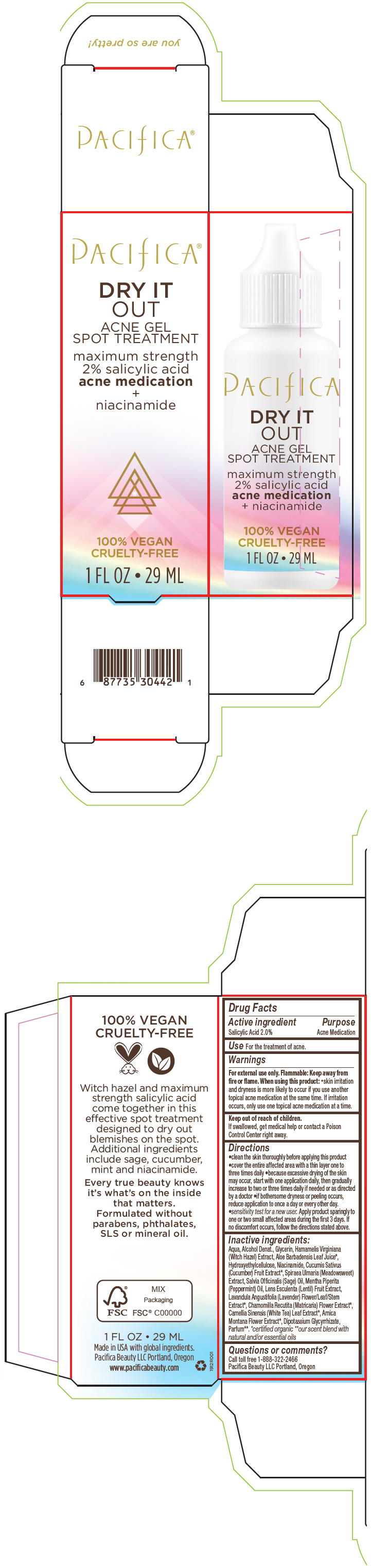 DRUG LABEL: DRY IT OUT ACNE SPOT TREATMENT
NDC: 61197-102 | Form: GEL
Manufacturer: Pacifica Beauty LLC.
Category: otc | Type: HUMAN OTC DRUG LABEL
Date: 20200106

ACTIVE INGREDIENTS: Salicylic Acid 20 mg/1 mL
INACTIVE INGREDIENTS: Water; Alcohol; Glycerin; Hamamelis Virginiana Top; Aloe Vera Leaf; Niacinamide; Cucumber; Sage Oil; Peppermint Oil; Lens Culinaris Fruit; Lavandula Angustifolia Subsp. Angustifolia Flowering Top; Chamomile; White Tea; Arnica Montana Flower; Glycyrrhizinate Dipotassium

DRY IT OUT ACNE SPOT TREATMENT

Drug Facts

Active ingredient

Salicylic Acid 2.0%

Purpose

Acne Medication

Use

For the treatment of acne.

Warnings

For external use only. Flammable: Keep away from fire or flame.

When using this product

- skin irritation and dryness is more likely to occur if you use another topical acne medication at the same time. If irritation occurs, only use one topical acne medication at a time.

Keep out of reach of children.

If swallowed, get medical help or contact a Poison Control Center right away.

Directions

- clean the skin thoroughly before applying this product
- cover the entire affected area with a thin layer one to three times daily
- because excessive drying of the skin may occur, start with one application daily, then gradually increase to two or three times daily if needed or as directed by a doctor
- if bothersome dryness or peeling occurs, reduce application to once a day or every other day.
- sensitivity test for a new user. Apply product sparingly to one or two small affected areas during the first 3 days. If no discomfort occurs, follow the directions stated above.

Inactive ingredients

Aqua, Alcohol Denat., Glycerin, Hamamelis Virginiana (Witch Hazel) Extract, Aloe Barbadensis Leaf Juice [certified organic] , Hydroxyethylcellulose, Niacinamide, Cucumis Sativus (Cucumber) Fruit Extract, Spiraea Ulmaria (Meadowsweet) Extract, Salvia Officinalis (Sage) Oil, Mentha Piperita (Peppermint) Oil, Lens Esculenta (Lentil) Fruit Extract, Lavandula Angustifolia (Lavender) Flower/Leaf/Stem Extract, Chamomilla Recutita (Matricaria) Flower Extract, Camellia Sinensis (White Tea) Leaf Extract, Arnica Montana Flower Extract, Dipotassium Glycyrrhizate, Parfum [our scent blend with natural and/or essential oils] .

Questions or comments?

Call toll free 1-888-322-2466

Pacifica Beauty LLC Portland, Oregon

PRINCIPAL DISPLAY PANEL - 29 ML Tube Carton

PACIFICA®

DRY IT
OUT
ACNE GEL
SPOT TREATMENT

maximum strength
2% salicylic acid
acne medication
+
niacinamide

100% VEGAN
CRUELTY-FREE

1 FL OZ • 29 ML